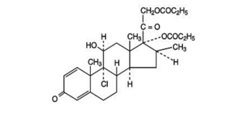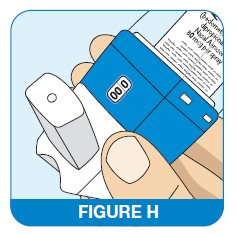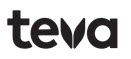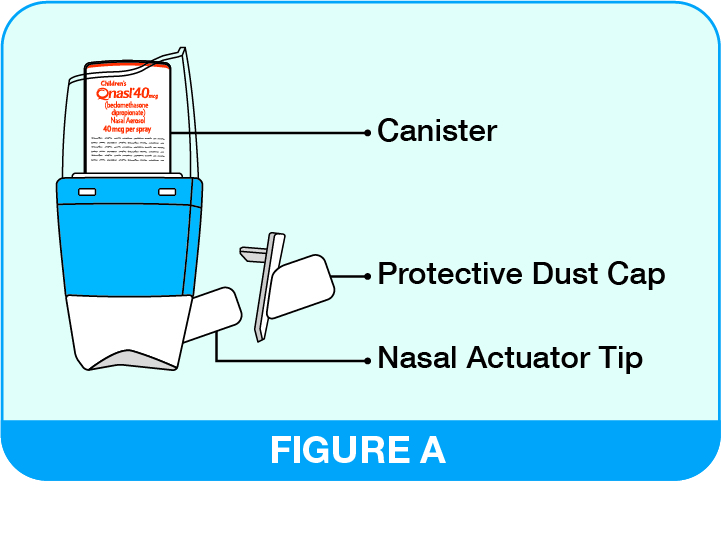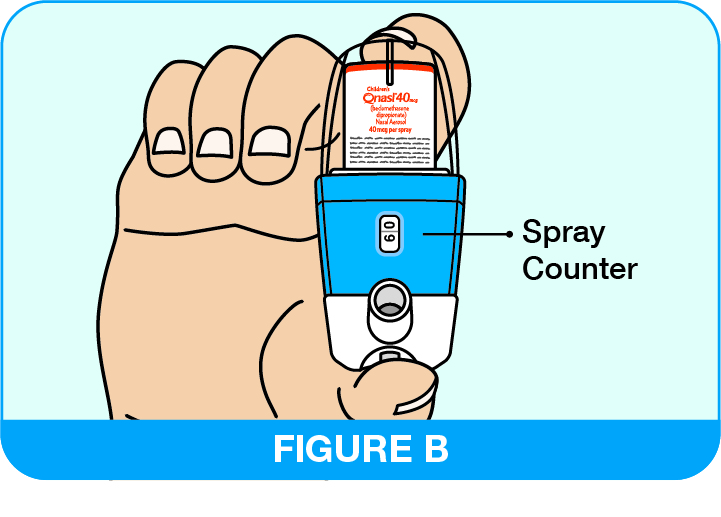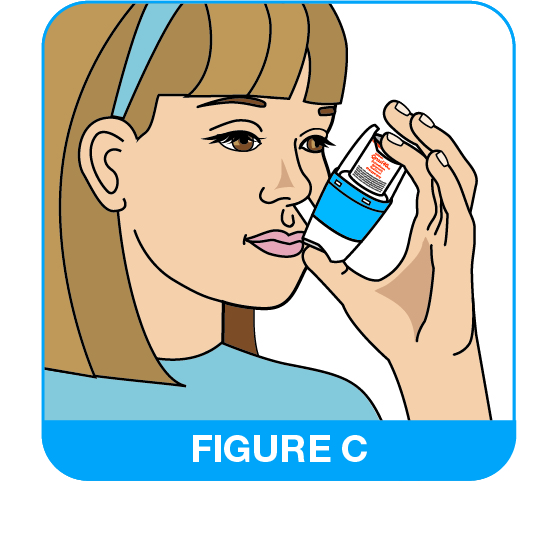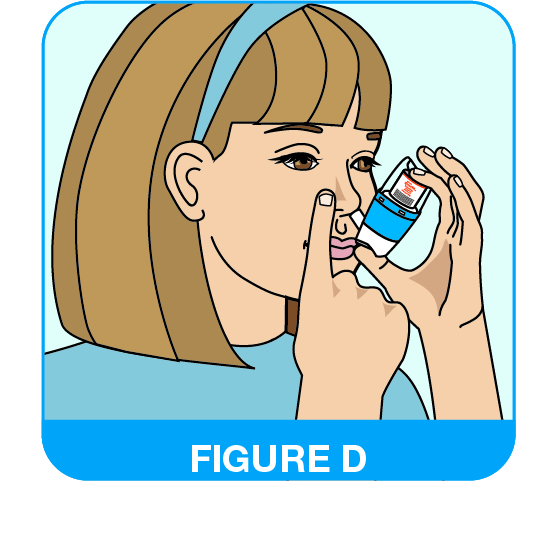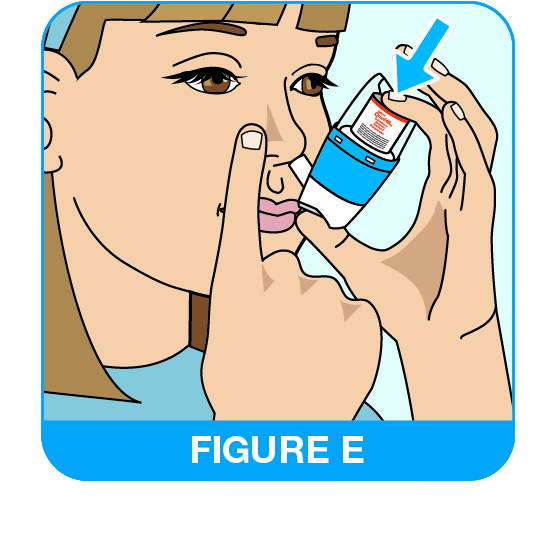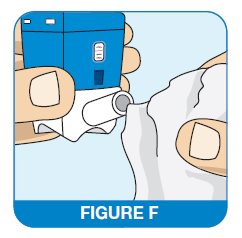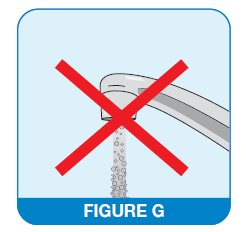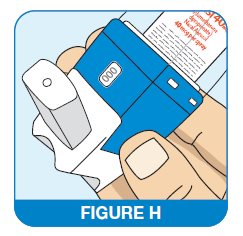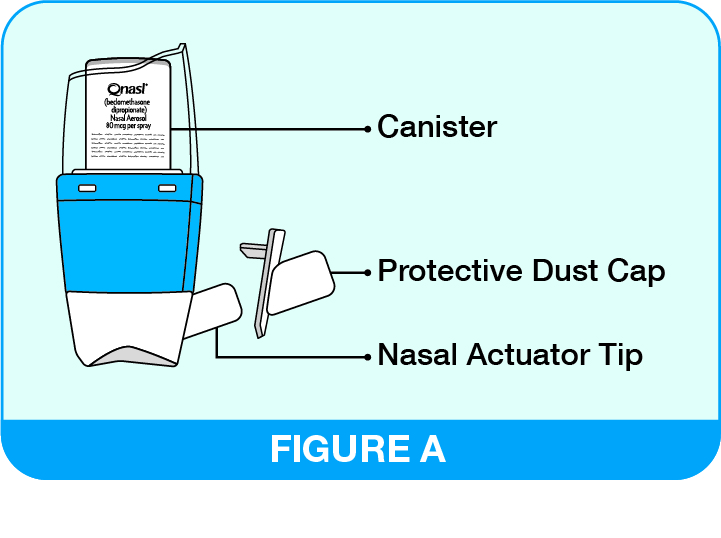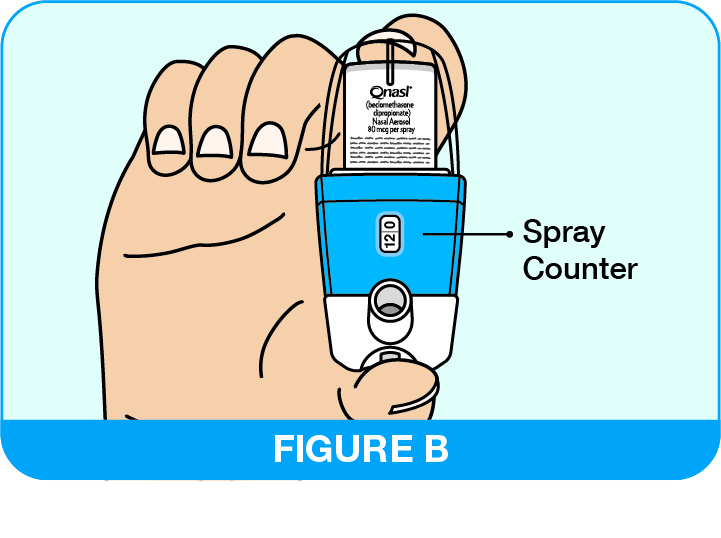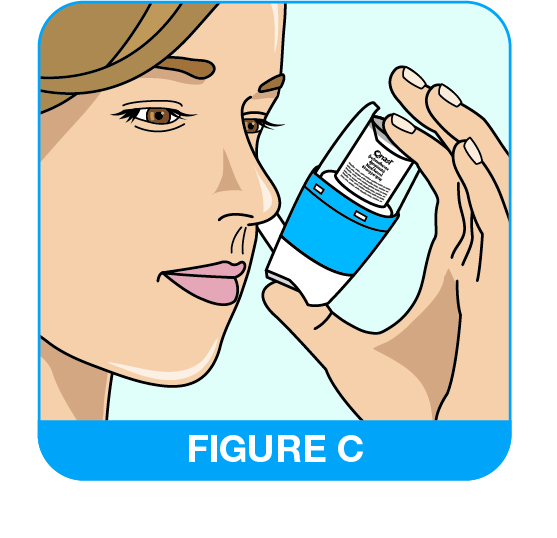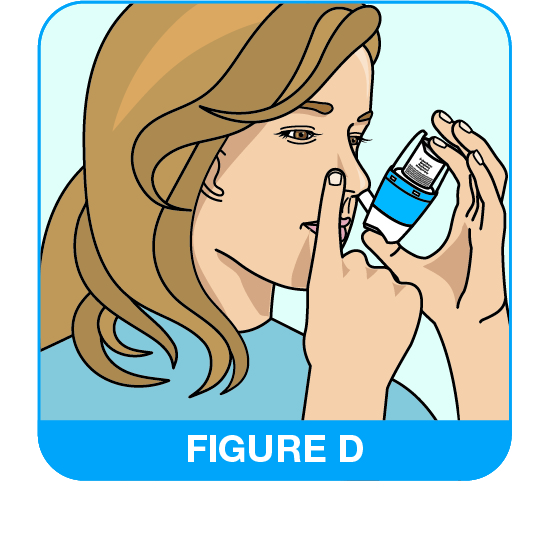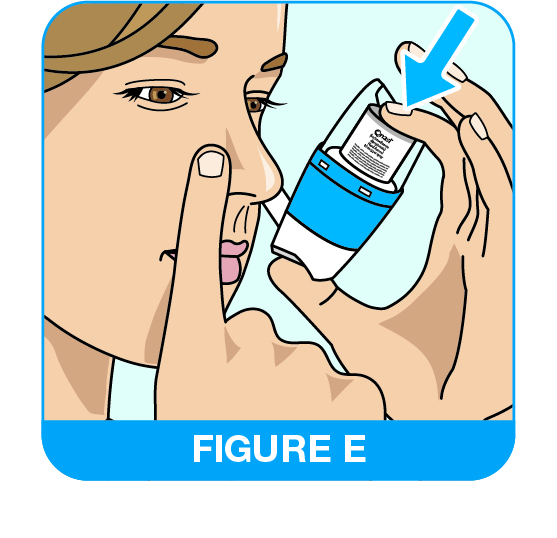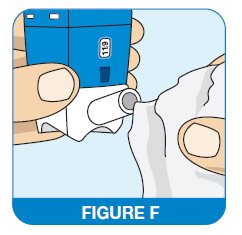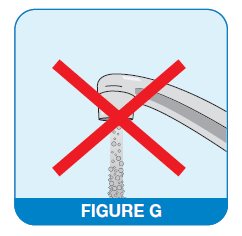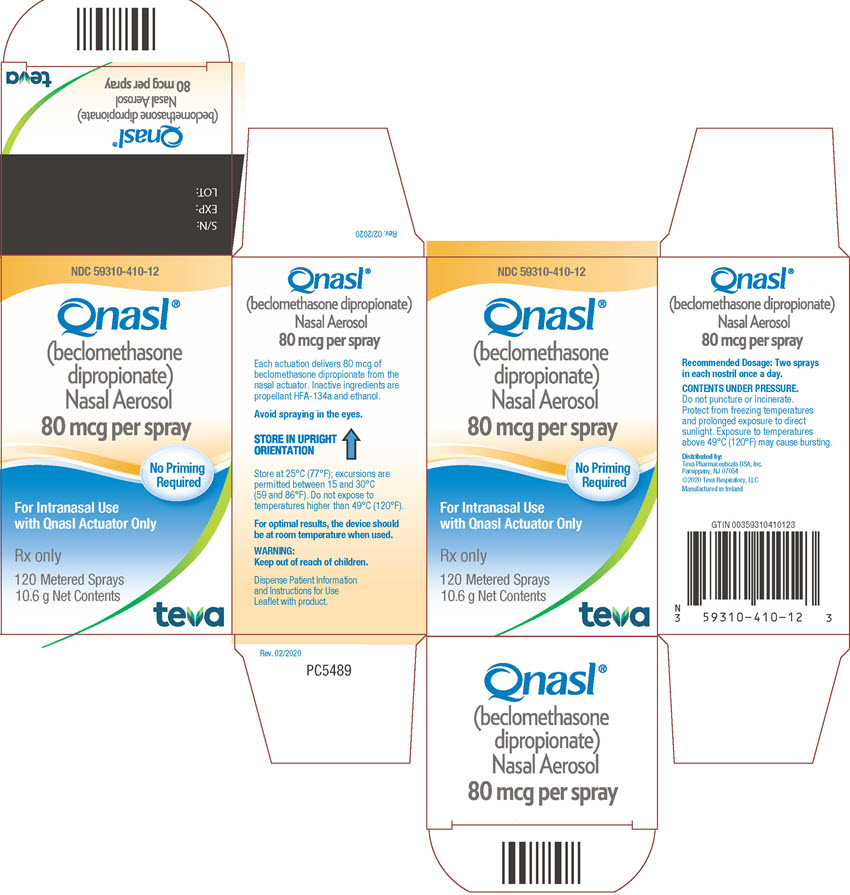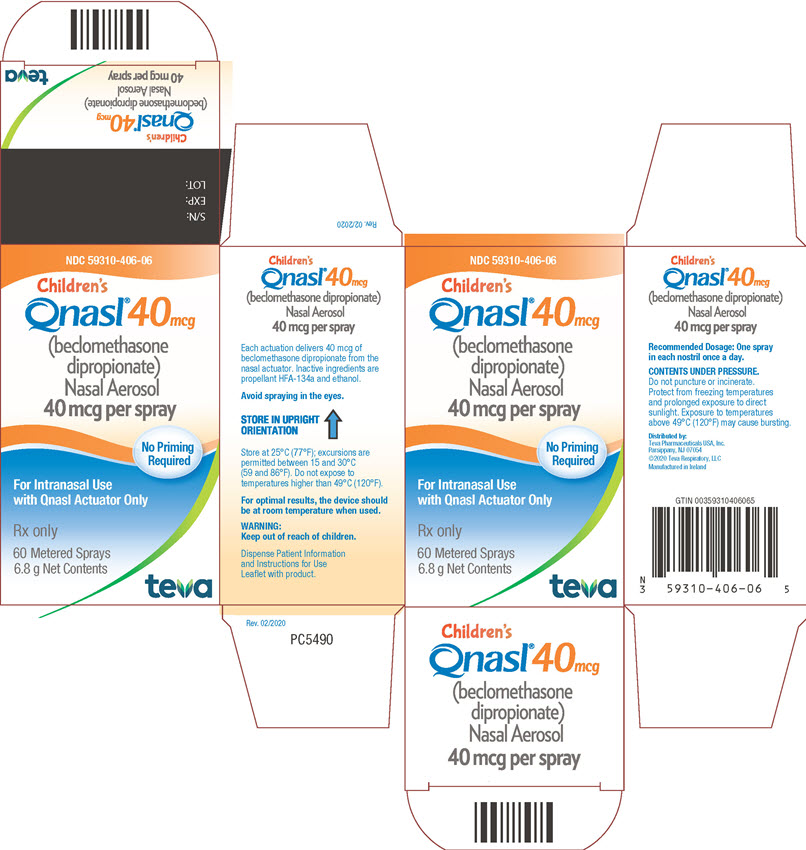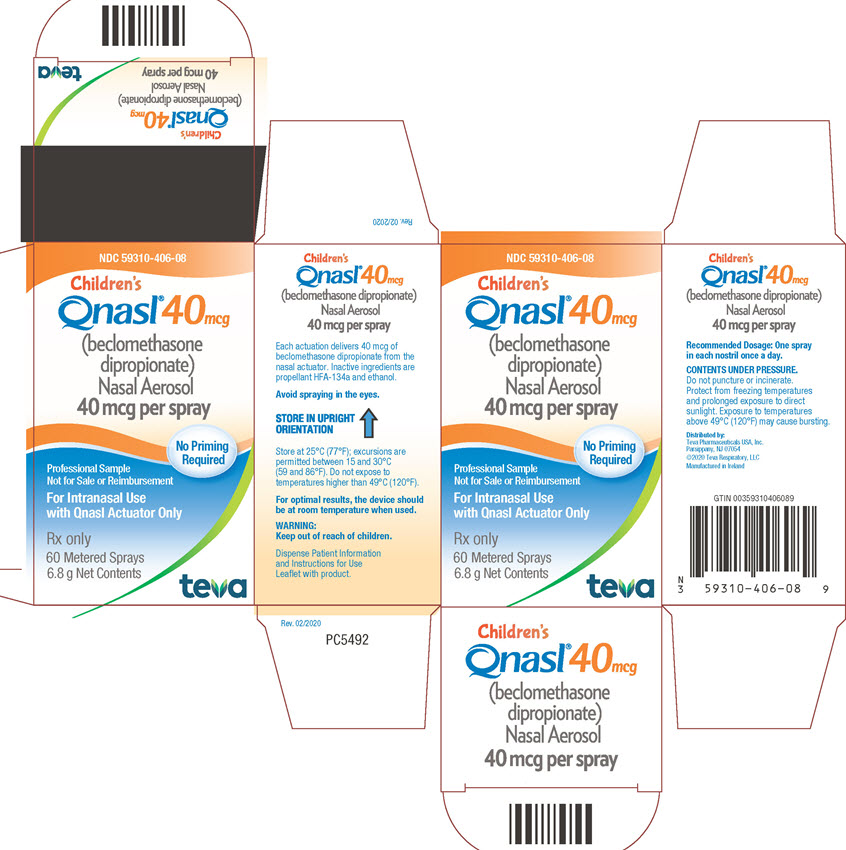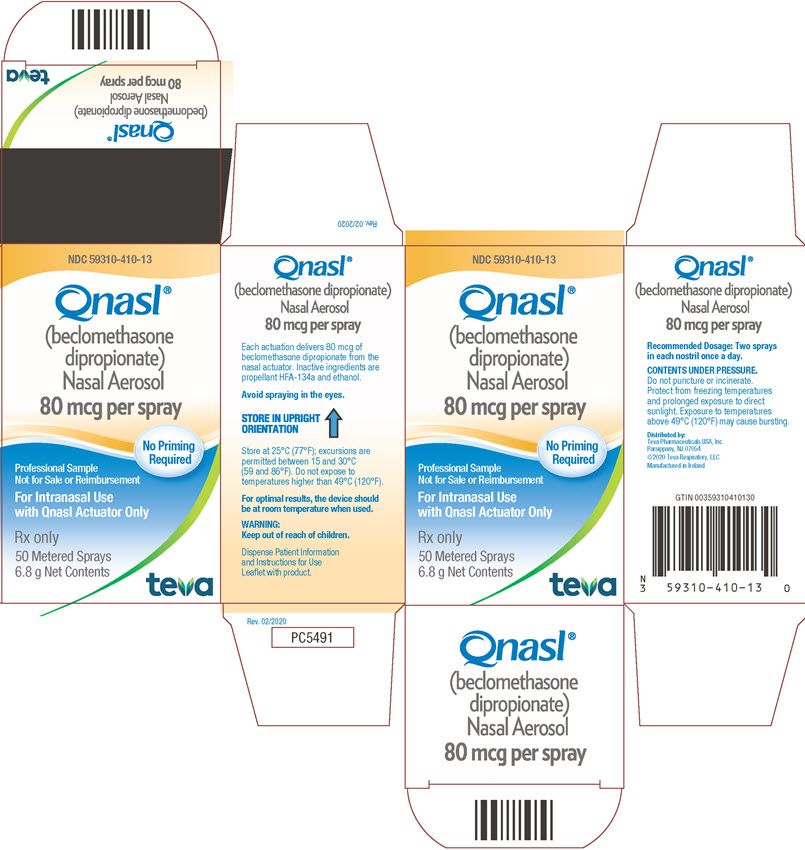 DRUG LABEL: QNASL
NDC: 59310-406 | Form: AEROSOL, METERED
Manufacturer: Teva Respiratory, LLC
Category: prescription | Type: HUMAN PRESCRIPTION DRUG LABEL
Date: 20220927

ACTIVE INGREDIENTS: BECLOMETHASONE DIPROPIONATE 40 ug/1 1
INACTIVE INGREDIENTS: NORFLURANE; ALCOHOL

HIGHLIGHTS OF PRESCRIBING INFORMATION

These highlights do not include all the information needed to use QNASL Nasal Aerosol safely and effectively. See full prescribing information for QNASL Nasal Aerosol.
QNASL® (beclomethasone dipropionate) Nasal Aerosol
For Intranasal Use Only
Initial U.S. Approval: 1976

1. INDICATIONS AND USAGE

QNASL Nasal Aerosol is a corticosteroid indicated for the treatment of nasal symptoms associated with seasonal and perennial allergic rhinitis in patients 4 years of age and older. (1.1)

2. DOSAGE AND ADMINISTRATION

QNASL Nasal Aerosol is for intranasal use only.

- The recommended dose of QNASL 80 mcg Nasal Aerosol in patients 12 years and older is 320 mcg per day administered as 2 actuations in each nostril once daily (maximum total daily dose of 4 actuations per day). (2.1)
- The recommended dose of QNASL 40 mcg Nasal Aerosol in children aged 4 to 11 years of age is 80 mcg per day administered as 1 actuation in each nostril once daily (maximum total daily dose of 2 actuations per day). (2.1)

3. DOSAGE FORMS AND STRENGTHS

QNASL Nasal Aerosol is available in two strengths:

- Each actuation of QNASL 80 mcg Nasal Aerosol delivers 80 mcg of beclomethasone dipropionate. (3)
- Each actuation of QNASL 40 mcg Nasal Aerosol delivers 40 mcg of beclomethasone dipropionate. (3)
- QNASL 80 mcg Nasal Aerosol is supplied in a 10.6 g canister containing 120 actuations; QNASL 40 mcg Nasal Aerosol is supplied in a 6.8 g canister containing 60 actuations. (3)

4. CONTRAINDICATIONS

Patients with a history of hypersensitivity to beclomethasone dipropionate and/or any other QNASL Nasal Aerosol ingredients. (4)

5. WARNINGS AND PRECAUTIONS

- Nasal discomfort, epistaxis, nasal ulceration, Candida albicans infection, nasal septal perforation, impaired wound healing. Monitor patients periodically for signs of adverse effects on the nasal mucosa. Avoid use in patients with recent nasal ulcers, nasal surgery, or nasal trauma. (5.1)
- Eye Disorders. Monitor patients closely with a change in vision or with a history of increased intraocular pressure, blurred vision, glaucoma, and/or cataracts. (5.2)
- Hypersensitivity, rash, and urticaria may occur after administration of QNASL Nasal Aerosol. (5.3)
- Potential worsening of existing tuberculosis; fungal, bacterial, viral, or parasitic infections; or ocular herpes simplex. More serious or even fatal course of chickenpox or measles in susceptible patients. Use caution in patients with the above because of the potential for worsening of these infections. (5.4)
- Hypercorticism and adrenal suppression with very high dosages or at the regular dosage in susceptible individuals. If such changes occur, discontinue QNASL Nasal Aerosol slowly. (5.5)
- Potential reduction in growth velocity in pediatric patients. Monitor growth routinely in pediatric patients receiving QNASL Nasal Aerosol. (5.6, 8.4)

6 ADVERSE REACTIONS

The most common adverse reactions (≥ 1% and greater than placebo) in patients 12 years of age and older include nasal discomfort, epistaxis, and headache. (6.1)

The most common adverse reactions (≥ 2% and greater than placebo) in children 4 to 11 years of age include headache, pyrexia, upper respiratory tract infection, and nasopharyngitis. (6.1)

To report SUSPECTED ADVERSE REACTIONS, contact Teva Pharmaceuticals at 1-888-482-9522 or FDA at 1-800-FDA-1088 or www.fda.gov/medwatch.

FULL PRESCRIBING INFORMATION

1. INDICATIONS AND USAGE

1.1 Treatment of Nasal Symptoms of Allergic Rhinitis

QNASL® Nasal Aerosol is indicated for the treatment of the nasal symptoms associated with seasonal and perennial allergic rhinitis in patients 4 years of age and older.

2. DOSAGE AND ADMINISTRATION

Administer QNASL Nasal Aerosol by the intranasal route only. The dose counter should read “120” for QNASL 80 mcg Nasal Aerosol 120-actuation product and “60” for QNASL 40 mcg Nasal Aerosol 60-actuation product. QNASL Nasal Aerosol does not require priming. See accompanying illustrated Patient Information and Instructions for Use leaflet for proper use of QNASL Nasal Aerosol.

2.1 Allergic Rhinitis

Adults and Adolescents (12 Years of Age and Older): The recommended dose of QNASL Nasal Aerosol is 320 mcg per day administered as 2 actuations in each nostril (QNASL 80 mcg Nasal Aerosol) once daily (maximum total daily dose of 4 actuations per day).

Children (4 to 11 Years of Age): The recommended dose of QNASL Nasal Aerosol is 80 mcg per day administered as 1 actuation in each nostril (QNASL 40 mcg Nasal Aerosol) once daily (maximum total daily dose of 2 actuations per day).

3. DOSAGE FORMS AND STRENGTHS

QNASL Nasal Aerosol is a nonaqueous nasal spray solution.

Each actuation of QNASL 80 mcg Nasal Aerosol delivers 80 mcg of beclomethasone dipropionate and each actuation of QNASL 40 mcg Nasal Aerosol delivers 40 mcg of beclomethasone dipropionate. QNASL 80 mcg Nasal Aerosol is supplied in a 10.6 g canister containing 120 actuations; QNASL 40 mcg Nasal Aerosol is supplied in a 6.8 g canister containing 60 actuations.

4. CONTRAINDICATIONS

QNASL Nasal Aerosol is contraindicated in patients with a history of hypersensitivity to beclomethasone dipropionate and/or any other QNASL Nasal Aerosol ingredients [see Warnings and Precautions (5.3)].

5. WARNINGS AND PRECAUTIONS

5.1 Local Nasal Effects

Nasal Discomfort, Epistaxis, and Nasal Ulceration: In clinical trials of 2 to 52 weeks duration, epistaxis and nasal ulcerations were observed more frequently and some epistaxis events were more severe in patients treated with QNASL Nasal Aerosol than those who received placebo. In the 52-week safety trial in patients with perennial allergic rhinitis, nasal erosions were identified in 4 of 415 patients and a nasal ulceration was identified in 1 of 415 patients treated with QNASL Nasal Aerosol. No nasal erosions or ulcerations were reported for patients who received placebo. In clinical trials conducted in pediatric patients ages 4 to 11 years, the local nasal effect was similar to those reported in patients 12 years of age and older. Patients using QNASL Nasal Aerosol over several months or longer should be examined periodically for possible changes in the nasal mucosa. If an adverse reaction (e.g., erosion, ulceration) is noted, discontinue QNASL Nasal Aerosol [see Adverse Reactions (6.1)].

Candida Infection: In previous clinical trials with an aqueous formulation of beclomethasone dipropionate administered intranasally, localized infections of the nose and pharynx with Candida albicans had been reported. There were no instances of similar infections observed in clinical trials with QNASL Nasal Aerosol. If such an infection develops, it may require treatment with appropriate local therapy and discontinuation of QNASL Nasal Aerosol treatment. Thus, patients using QNASL Nasal Aerosol over several months or longer should be examined periodically for evidence of Candida infection.

Nasal Septal Perforation: Instances of nasal septal perforation have been reported in patients following the intranasal application of beclomethasone dipropionate. There were no nasal septal perforations reported during clinical trials in the indicated dose of QNASL 80 mcg Nasal Aerosol administered as 320 mcg once daily in adults and adolescents. There was one report of nasal septal perforation observed in the dose-ranging pediatric clinical trial.

Impaired Wound Healing: Because of the inhibitory effect of corticosteroids on wound healing, patients who have experienced recent nasal septal ulcers, nasal surgery, or nasal trauma should not use QNASL Nasal Aerosol until healing has occurred.

5.2 Eye Disorders

Use of intranasal and inhaled corticosteroids may result in the development of increased intraocular pressure, blurred vision, glaucoma and/or cataracts. Therefore, close monitoring is warranted in patients with a change in vision or with a history of increased intraocular pressure, blurred vision, glaucoma, and/or cataracts.

Glaucoma and cataract formation was evaluated with ocular assessments that included intraocular pressure measurements and slit lamp examinations in 245 adolescent and adult patients (12 years of age and older) with perennial allergic rhinitis who were treated with QNASL Nasal Aerosol 320 mcg daily (N=197) or placebo (N=48) for up to 52 weeks. In 94% of patients, intraocular pressure (IOP) remained within the normal range (<21 mmHg) during the treatment portion of the trial. There were 10 patients (5%) treated with QNASL Nasal Aerosol and 1 patient (2%) treated with placebo that had intraocular pressure that increased above normal levels (≥21 mmHg) and greater than baseline during the treatment portion of the trial. Two of these occurrences in patients treated with QNASL Nasal Aerosol were reported as adverse reactions, one serious. No instances of cataract formation or other clinically significant ocular incidents were reported in this 52-week safety trial [see Adverse Reactions (6.1)].

5.3 Hypersensitivity Reactions Including Anaphylaxis

Hypersensitivity reactions including anaphylaxis, angioedema, urticaria, and rash have been reported following administration of beclomethasone dipropionate nasally administered and inhalationally administered products. Angioedema, urticaria, and rash have been reported following administration of QNASL Nasal Aerosol. Discontinue QNASL Nasal Aerosol if any such reactions occur [see Contraindications (4)].

5.4 Immunosuppression

Persons who are using drugs that suppress the immune system (e.g., corticosteroids) are more susceptible to infections than healthy individuals. Chickenpox and measles, for example, can have a more serious or even fatal course in susceptible children or adults using corticosteroids. In children or adults who have not had these diseases or been properly immunized, particular care should be taken to avoid exposure. How the dose, route, and duration of corticosteroid administration affect the risk of developing a disseminated infection is not known. The contribution of the underlying disease and/or prior corticosteroid treatment to the risk is also not known. If a patient is exposed to chickenpox, prophylaxis with varicella zoster immune globulin (VZIG) may be indicated. If a patient is exposed to measles, prophylaxis with pooled intramuscular immunoglobulin (IG) may be indicated (see the respective package inserts for complete VZIG and IG prescribing information). If chickenpox or measles develops, treatment with antiviral agents may be considered.

Corticosteroids should be used with caution, if at all, in patients with active or quiescent tuberculous infections of the respiratory tract, untreated local or systemic fungal or bacterial infections, systemic viral or parasitic infections, or ocular herpes simplex because of the potential for worsening of these infections.

5.5 Hypothalamic-Pituitary-Adrenal Axis Effect

When intranasal steroids are used at higher-than-recommended dosages or in susceptible individuals at recommended dosages, systemic corticosteroid effects such as hypercorticism and adrenal suppression may appear. If such changes occur, the dosage of QNASL Nasal Aerosol should be discontinued slowly, consistent with accepted procedures for discontinuing oral corticosteroid therapy.

The replacement of a systemic corticosteroid with a topical corticosteroid can be accompanied by signs of adrenal insufficiency. In addition, some patients may experience symptoms of corticosteroid withdrawal (e.g., joint and/or muscular pain, lassitude, and depression). Patients previously treated for prolonged periods with systemic corticosteroids and transferred to topical corticosteroids should be carefully monitored for acute adrenal insufficiency in response to stress. In patients who have asthma or other clinical conditions requiring long-term systemic corticosteroid treatment, rapid decreases in systemic corticosteroid dosages may cause a severe exacerbation of their symptoms.

5.6 Effect on Growth

Corticosteroids may cause a reduction in growth velocity when administered to pediatric patients. Routinely monitor the growth of pediatric patients receiving QNASL Nasal Aerosol [see Use in Specific Populations (8.4)].

6 ADVERSE REACTIONS

Systemic and local corticosteroid use may result in the following:

- Epistaxis, nasal discomfort, nasal ulcerations, Candida albicans infection, and impaired wound healing [see Warnings and Precautions (5.1)]
- Eye Disorders [see Warnings and Precautions (5.2)]
- Hypercorticism, adrenal suppression, and growth reduction [see Warnings and Precautions (5.5) (5.6), Use in Specific Populations (8.4)]
- Immunosuppression [see Warnings and Precautions (5.4)]

6.1 Clinical Trials Experience

Because clinical trials are conducted under widely varying conditions, adverse reaction rates observed in the clinical trials of a drug cannot be directly compared with rates in the clinical trials of another drug and may not reflect the rates observed in practice.

Adults and Adolescents 12 Years of Age and Older:

The safety data described below for adults and adolescents 12 years of age and older with seasonal or perennial allergic rhinitis are based on 4 placebo-controlled clinical trials of 2 to 6 weeks duration evaluating doses of beclomethasone nasal aerosol from 80 to 320 mcg once daily. These short-term trials included a total of 1394 patients with either seasonal or perennial allergic rhinitis. Of these, 575 (378 female and 197 male) received at least one dose of QNASL Nasal Aerosol, 320 mcg once daily and 578 (360 female and 218 male) received placebo. Patient ages ranged from 12 to 82 years and the racial distribution of patients was 81% white, 16% black, and 4% other.

Short-Term (2–6 Weeks) Trials: Less than 2% of patients in the clinical trials discontinued treatment because of adverse reactions with the rate of withdrawal among patients who received QNASL Nasal Aerosol similar to or lower than the rate among patients who received placebo. Table 1 displays the common adverse reactions (≥ 1% and greater than placebo-treated patients).

Table 1. Adverse Events With ³ 1% Incidence and Greater than Placebo in QNASL Nasal Aerosol-Treated Adult and Adolescent Patients with Seasonal or Perennial Allergic Rhinitis in Controlled Clinical Trials of 2 to 6 Weeks Duration (Safety Population)
 | Adult and Adolescent Patients 12 Years of Age and Older
 | QNASL Nasal Aerosol; 320 mcg; (N=575); n (%) | Placebo; (N=578); n (%)
Nasal Discomfort | 30 (5.2) | 28 (4.8)
Epistaxis | 11 (1.9) | 7 (1.2)
Headache | 13 (2.3) | 9 (1.6)

Nasal ulcerations occurred in 2 patients treated with placebo and in 1 patient treated with QNASL Nasal Aerosol. There were no differences in the incidence of adverse reactions based on gender or race. Clinical trials did not have sufficient numbers of patients aged 65 years and older to determine whether they respond differently than younger patients.

Long-Term 52-Week Safety Trial: In a 52-week placebo-controlled long-term safety trial in patients with PAR, 415 patients (128 males and 287 females, aged 12 to 74 years) were treated with QNASL Nasal Aerosol at a dose of 320 mcg once daily and 111 patients (44 males and 67 females, aged 12 to 67 years) were treated with placebo. Of the 415 patients treated with QNASL Nasal Aerosol, 219 patients were treated for 52 weeks and 196 patients were treated for 30 weeks. While most adverse events were similar in type and rate between the treatment groups, epistaxis occurred more frequently in patients who received QNASL Nasal Aerosol (45 out of 415, 11%) than in patients who received placebo (2 out of 111, 2%). Epistaxis also tended to be more severe in patients treated with QNASL Nasal Aerosol. In 45 reports of epistaxis in patients who received QNASL Nasal Aerosol, 27, 13, and 5 cases were of mild, moderate, and severe intensity, respectively, while the reports of epistaxis in patients who received placebo were of mild (1) and moderate (1) intensity. Seventeen patients treated with QNASL Nasal Aerosol experienced adverse reactions that led to withdrawal from the trial compared to 3 patients treated with placebo. There were 4 nasal erosions and 1 nasal septum ulceration which occurred in patients who received QNASL Nasal Aerosol, and no erosions or ulcerations noted in patients who received placebo. No patient experienced a nasal septum perforation during the trial.

Pediatric Patients Aged 4 to 11 Years:

The safety data described below for pediatric patients 4 to 11 years of age with seasonal or perennial allergic rhinitis are based on 3 placebo-controlled clinical trials. These trials were 2 to 12 weeks in duration, evaluated doses of beclomethasone nasal aerosol 80 mcg to 160 mcg once daily and included a total of 1360 patients with either seasonal or perennial allergic rhinitis. Of these, 668 (312 female and 356 male) received at least one dose of QNASL Nasal Aerosol, 80 mcg once daily, 241 (116 female and 125 male) received QNASL Nasal Aerosol 160 mcg once daily, and 451 (203 female and 248 male) received placebo. The racial distribution of patients was 73% white, 20% black, and 6% other. Based on the results from the dose ranging trial, 80 mcg once daily was chosen as the dose in pediatric patients.

Less than 1.5% of patients in the clinical trials discontinued treatment because of adverse reactions with the rate of withdrawal among patients who received QNASL Nasal Aerosol 80 mcg once daily similar to or lower than the rate among patients who received placebo. Table 2 displays the common adverse reactions (≥ 2% and greater than placebo-treated patients). Additionally, epistaxis was reported at a rate of 4% for both QNASL Nasal Aerosol 80 mcg once daily and placebo-treated patients.

Table 2. Adverse Events With ≥ 2% Incidence and Greater than Placebo in QNASL Nasal Aerosol-Treated Pediatric Patients with Seasonal or Perennial Allergic Rhinitis in Controlled Clinical Trials of 2 to 12 weeks Duration (Safety Population)
 | Pediatric Patients 4 to 11 Years of Age
 | QNASL Nasal Aerosol 80 mcg (N=668); n (%) | Placebo; (N=451); n (%)
Headache | 23 (3.4) | 15 (3.3)
Pyrexia | 19 (2.8) | 7 (1.6)
Upper respiratory tract infection | 17 (2.5) | 8 (1.8)
Nasopharyngitis | 15 (2.2) | 6 (1.3)

6.2 Postmarketing Experience

In addition to adverse reactions reported from clinical trials for QNASL Nasal Aerosol, the following adverse events have been reported during postmarketing use of QNASL Nasal Aerosol or other intranasal and inhaled formulations of beclomethasone dipropionate. Because these reactions are reported voluntarily from a population of uncertain size, it is not always possible to reliably estimate their frequency or establish a causal relationship to drug exposure. These events have been chosen for inclusion due to either their seriousness, frequency of reporting, or causal connection to beclomethasone dipropionate or a combination of these factors.

QNASL Nasal Aerosol: sneezing, burning sensation

Intranasal beclomethasone dipropionate: Nasal septal perforation, blurred vision, glaucoma, cataracts, central serous chorioretinopathy (CSC), loss of taste and smell, and hypersensitivity reactions including anaphylaxis, angioedema, rash, and urticaria have been reported following intranasal administration of beclomethasone dipropionate.

Inhaled beclomethasone dipropionate: Hypersensitivity reactions, including anaphylaxis, angioedema, rash, urticaria, and bronchospasm have been reported following the oral inhalation of beclomethasone dipropionate.

7 DRUG INTERACTIONS

No drug interaction studies have been performed with QNASL Nasal Aerosol.

8 USE IN SPECIFIC POPULATIONS

8.1 Pregnancy

Risk Summary

There are no adequate and well-controlled studies with QNASL Nasal Aerosol or beclomethasone dipropionate in pregnant women. No published studies, including studies of large birth registries, have to date related the use of inhaled corticosteroids (ICS) or intranasal corticosteroids to any increases in congenital malformations or other adverse perinatal outcomes. Thus, available human data do not establish the presence or absence of drug‑associated risk to the fetus. In animal reproduction studies, beclomethasone dipropionate resulted in adverse developmental effects in mice and rabbits at subcutaneous doses equal to or greater than approximately 1.5 times the maximum recommended human dose (MRHD) in adults (0.32 mg/day) (see Data). In rats exposed to beclomethasone dipropionate by inhalation, dose‑related gross injury to the fetal adrenal glands was observed at doses greater than 350 times the MRHD, but there was no evidence of external or skeletal malformations or embryolethality at inhalation doses of up to 860 times the MRHD.

The estimated background risk of major birth defects and miscarriage for the indicated population(s) are unknown. In the US general population, the estimated risk of major birth defects and miscarriage in clinically recognized pregnancies is 2‑4% and 15‑20%, respectively.

Clinical Considerations

Labor or Delivery

There are no specific human data regarding any adverse effects of intranasal beclomethasone dipropionate on labor and delivery.

Data

Animal Data

In an embryofetal development study in pregnant rats, beclomethasone dipropionate administration during organogenesis from gestation days 6 to 15 at inhaled doses 350 times the MRHD in adults and higher (on a mg/m^2 basis at maternal doses of 11.5 and 28.3 mg/kg/day) produced dose‑dependent gross injury (characterized by red foci) of the adrenal glands in fetuses. There were no findings in the adrenal glands of rat fetuses at an inhaled dose that was 75 times the MRHD in adults (on a mg/m^2 basis at a maternal dose of 2.4 mg/kg/day). There was no evidence of external or skeletal malformations or embryolethality in rats at inhaled doses up to 860 times the MRHD (on a mg/m^2 basis at maternal doses up to 28.3 mg/kg/day).

In an embryofetal development study in pregnant mice, beclomethasone dipropionate administration from gestation days 1 to 18 at subcutaneous doses equal to and greater than 1.5 times the MRHD in adults (on a mg/m^2 basis at maternal doses of 0.1 mg/kg/day and higher) produced adverse developmental effects (increased incidence of cleft palate). A no-effect dose in mice was not identified. In a second embryofetal development study in pregnant mice, beclomethasone dipropionate administration from gestation days 1 to 13 at subcutaneous doses equal to and greater than 5 times the MRHD in adults (on a mg/m^2 basis at a maternal dose of 0.3 mg/kg/day) produced embryolethal effects (increased fetal resorptions) and decreased pup survival.

In an embryofetal development study in pregnant rabbits, beclomethasone dipropionate administration during organogenesis from gestation days 7 to 16 at subcutaneous doses equal to and greater than 1.5 times the MRHD in adults (on a mg/m^2 basis at maternal doses of 0.025 mg/kg/day and higher) produced external and skeletal malformations and embryolethal effects (increased fetal resorptions). There were no effects in fetuses of pregnant rabbits administered a subcutaneous dose 0.4 times the MRHD in adults (on a mg/m^2 basis at a maternal dose of 0.006 mg/kg/day).

8.2 Lactation

Risk Summary

There are no data available on the presence of beclomethasone dipropionate in human milk, the effects on the breastfed child, or the effects on milk production. However, other corticosteroids have been detected in human milk. The developmental and health benefits of breastfeeding should be considered along with the mother’s clinical need for QNASL and any potential adverse effects on the breastfed child from beclomethasone dipropionate or from the underlying maternal condition.

8.3 Females and Males of Reproductive Potential

Impairment of fertility was observed in rats and dogs at oral doses of beclomethasone dipropionate corresponding to 500 and 50 times the MRHD for adults on a mg/m^2 basis, respectively. [see Nonclinical Toxicology (13.1)].

8.4 Pediatric Use

The safety and effectiveness of QNASL Nasal Aerosol in children 4 years and older have been established [see Adverse Reactions (6.1), Clinical Pharmacology (12.3), Clinical Studies (14)]. The safety and effectiveness of QNASL Nasal Aerosol in children younger than 4 years of age have not been established. Controlled pediatric clinical trials with QNASL Nasal Aerosol included 909 children 4 to 11 years of age and 188 adolescent patients 12 to 17 years of age [see Clinical Studies (14)].

Controlled clinical trials have shown that intranasal corticosteroids may cause a reduction in growth velocity in pediatric patients. This effect has been observed in the absence of laboratory evidence of hypothalamic-pituitary-adrenal (HPA) axis suppression, suggesting that growth velocity is a more sensitive indicator of systemic corticosteroid exposure in pediatric patients than some commonly used tests of HPA-axis function. The long-term effects of reduction in growth velocity associated with intranasal corticosteroids, including the impact on final adult height, are unknown. The potential for "catch-up" growth following discontinuation of treatment with intranasal corticosteroids has not been adequately studied. The growth of pediatric patients receiving intranasal corticosteroids, including QNASL Nasal Aerosol, should be monitored routinely (e.g., via stadiometry).

A 12-month, randomized, controlled clinical trial evaluated the effects of QVAR®, an orally inhaled HFA beclomethasone dipropionate product, without spacer versus chlorofluorocarbon-propelled (CFC) beclomethasone dipropionate with large volume spacer on growth in children with asthma ages 5 to 11 years. A total of 520 patients were enrolled, of whom 394 received HFA-beclomethasone dipropionate (100 to 400 mcg/day ex-valve) and 126 received CFC-beclomethasone dipropionate (200 to 800 mcg/day ex-valve). When comparing results at month 12 to baseline, the mean growth velocity in children treated with HFA-beclomethasone dipropionate was approximately 0.5 cm/year less than that noted with children treated with CFC-beclomethasone dipropionate via large volume spacer. The potential growth effects of prolonged treatment should be weighed against the clinical benefits obtained and the risks/benefits of treatment alternatives.

The potential for QNASL Nasal Aerosol to cause reduction in growth velocity in susceptible patients or when given at higher than recommended dosages cannot be ruled out.

8.5 Geriatric Use

Clinical trials of QNASL Nasal Aerosol did not include sufficient numbers of subjects aged 65 years and older to determine whether they responded differently than younger subjects. Other reported clinical experience has not identified differences in responses between the elderly and younger patients. In general, administration to elderly patients should be cautious, reflecting the greater frequency of decreased hepatic, renal, or cardiac function, and of concomitant disease or other drug therapy.

10 OVERDOSAGE

Chronic overdosage may result in signs/symptoms of hypercorticism [see Warnings and Precautions (5.5)]. There are no data available on the effects of acute or chronic overdosage with QNASL Nasal Aerosol.

11 DESCRIPTION

Beclomethasone dipropionate USP, the active component of QNASL Nasal Aerosol, is an anti-inflammatory steroid having the chemical name 9-chloro-11β,17,21-trihydroxy-16β-methylpregna-1,4-diene-3,20-dione 17, 21-dipropionate and the following chemical structure:

Beclomethasone dipropionate, a di-ester of beclomethasone (a synthetic corticosteroid chemically related to dexamethasone), is a white to almost white, odorless powder with a molecular formula of C28H37ClO7 and a molecular weight of 521.1. It is practically insoluble in water, very soluble in chloroform, and soluble in acetone and in dehydrated alcohol.

QNASL Nasal Aerosol is a pressurized, nonaqueous solution in a metered-dose aerosol device intended ONLY for intranasal use. It contains a solution of beclomethasone dipropionate in propellant HFA‑134a (1,1,1,2‑tetrafluoroethane) and dehydrated ethanol. QNASL 40 mcg Nasal Aerosol delivers 40 mcg of beclomethasone dipropionate from the nasal actuator and 50 mcg from the valve. QNASL 80 mcg Nasal Aerosol delivers 80 mcg of beclomethasone dipropionate from the nasal actuator and 100 mcg from the valve. Each strength delivers 59 mg of solution from the valve with each actuation. Each QNASL 80 mcg Nasal Aerosol canister contains 10.6 g of drug and excipients and provides 120 actuations. Each QNASL 40 mcg Nasal Aerosol canister contains 6.8 g of drug and excipients and provides 60 actuations.

12 CLINICAL PHARMACOLOGY

12.1 Mechanism of Action

Beclomethasone dipropionate is a prodrug that is extensively converted to the active metabolite, beclomethasone-17-monopropionate. The precise mechanism through which beclomethasone dipropionate affects rhinitis symptoms is unknown. Corticosteroids have been shown to have multiple anti-inflammatory effects, inhibiting both inflammatory cells (e.g., mast cells, eosinophils, basophils, lymphocytes, macrophages, and neutrophils) and the release of inflammatory mediators (e.g., histamine, eicosanoids, leukotrienes, and cytokines).

Beclomethasone-17-monopropionate has been shown in vitro to exhibit a binding affinity for the human glucocorticoid receptor which is approximately 13 times that of dexamethasone, 6 times that of triamcinolone acetonide, 1.5 times that of budesonide and 25 times that of beclomethasone dipropionate. The clinical significance of these findings is unknown.

12.2 Pharmacodynamics

Adrenal Function: The effects of QNASL Nasal Aerosol on the HPA axis were evaluated in two 6-week, randomized, double-blind, parallel-group perennial allergic rhinitis trials – one in adult and adolescent patients 12 to 45 years of age and another in children 6 to 11 years of age. In the first study with adolescent and adult patients aged 12 to 45, QNASL Nasal Aerosol 320 mcg, once daily, was compared with both placebo nasal aerosol and a positive control (a placebo/prednisone group that received prednisone 10 mg orally once daily for the final 7 days of the treatment period). In the second study with pediatric patients aged 6 to 11, QNASL Nasal Aerosol 80 mcg once daily was compared to placebo nasal aerosol. HPA-axis function was assessed by 24-hour serial serum cortisol levels prior to the first dose and after 6 weeks of treatment. Patients were domiciled for the 24-hour serum cortisol assessments. The change from baseline in the 24-hour serum cortisol weighted mean for QNASL Nasal Aerosol and placebo after 6 weeks of treatment were compared.

In the HPA–axis study in patients 12 to 45 years of age, baseline geometric mean serum cortisol weighted mean values were similar in the QNASL Nasal Aerosol 320 mcg/day and placebo treatment groups (9.04 and 8.45 mcg/dL, respectively). After 6 weeks of treatment, the geometric mean values were 8.18 and 8.01 mcg/dL, respectively, with a change from baseline in 24-hour serum cortisol weighted mean for the QNASL Nasal Aerosol and placebo groups of 0.86 and 0.44, resulting in a difference of 0.42. The geometric mean ratio for QNASL Nasal Aerosol 320 mcg/day to placebo was 0.96 (95% CI: 0.87, 1.06). For comparison, in the positive-control (prednisone) treatment group, the geometric mean ratio for placebo to placebo/prednisone 10 mg/day was 3.17 (95% CI: 2.68, 3.74).

In the HPA-axis study in patients 6 to 11 years of age, baseline geometric mean serum cortisol weighted mean values were similar in the QNASL Nasal Aerosol 80 mcg/day and placebo treatment groups (5.97 and 6.47 mcg/dL, respectively). After 6 weeks of treatment the geometric mean values were 6.19 and 7.13 mcg/dL, respectively with no decrease from baseline values in both treatment groups. The geometric mean ratio for QNASL Nasal Aerosol 80 mcg/day to placebo was 0.91 (95% CI; 0.81, 1.03).

12.3 Pharmacokinetics

Absorption

Following intranasal administration, most of the beclomethasone dipropionate undergoes extensive conversion to its active metabolite, beclomethasone-17-monopropionate, during absorption. Plasma concentrations of beclomethasone dipropionate and beclomethasone-17-monopropionate have been measured with QNASL Nasal Aerosol in 2 adult and/or adolescent clinical trials and 1 pediatric clinical trial.

The single-dose pharmacokinetics of QNASL Nasal Aerosol were evaluated in a randomized, open-label, 3-period, crossover trial in healthy adult volunteers. Systemic levels of beclomethasone-17-monopropionate and beclomethasone dipropionate after single-dose intranasal administration of beclomethasone dipropionate at doses of 80 and 320 mcg were compared with the systemic levels of beclomethasone-17-monopropionate and beclomethasone dipropionate after administration of orally inhaled beclomethasone dipropionate HFA at a dose of 320 mcg (QVAR® Inhalation Aerosol). The results of this trial demonstrated that the systemic bioavailability of QNASL Nasal Aerosol 320 mcg was approximately 27.5% (approximately 4-fold lower) of that of orally inhaled beclomethasone dipropionate HFA 320 mcg/day based on the plasma concentrations of beclomethasone-17-monopropionate (AUClast: 1139.7 vs 4140.3 hr*pg/mL; GMR: 0.275; 90% CI for the GMR: 0.214, 0.354). The peak exposure to QNASL Nasal Aerosol 320 mcg/day was approximately 19.5% (approximately 5-fold lower) of that of orally inhaled beclomethasone dipropionate HFA 320 mcg/day as measured by beclomethasone-17-monopropionate (Cmax: 262.7 vs 1343.7 pg/mL; GMR: 0.195; 90% CI for the GMR: 0.158, 0.241).

Following repeated once-daily administration of QNASL Nasal Aerosol, there was no accumulation or increase in plasma exposure to beclomethasone-17-monopropionate or beclomethasone dipropionate, most likely due to the short plasma half-life relative to the dosing frequency.

Distribution

The in vitro protein binding for beclomethasone-17-monopropionate was reported to be 94% to 96% over the concentration range of 1000 to 5000 pg/mL. The volume of distribution at steady state for beclomethasone dipropionate is moderate (20 L) but more extensive for beclomethasone-17-monopropionate (424 L).

Metabolism

Beclomethasone dipropionate undergoes extensive first-pass metabolism, forming three metabolites via CYP3A4, beclomethasone-17-monopropionate, beclomethasone-21-monopropionate, and beclomethasone. Beclomethasone-17-monopropionate is the major and most active metabolite.

Elimination

The major route of elimination of inhaled beclomethasone dipropionate appears to be via metabolism. More than 90% of inhaled beclomethasone dipropionate is found as beclomethasone-17-monopropionate in the systemic circulation. The mean elimination half-life of beclomethasone-17-monopropionate is 2.8 hours. The terminal elimination half-lives of beclomethasone dipropionate and beclomethasone-17-monopropionate following intranasal dosing with QNASL Nasal Aerosol (320 mcg) were approximately 0.3 hours and 4.5 hours, respectively. Irrespective of the route of administration (injection, oral, or inhalation), beclomethasone dipropionate and its metabolites are mainly excreted in the feces. Less than 10% of the drug and its metabolites are excreted in the urine. It is likely that intranasal beclomethasone dipropionate follows a similar elimination pathway.

Special Populations

Formal pharmacokinetic studies using QNASL Nasal Aerosol were not conducted in any special populations.

13 NONCLINICAL TOXICOLOGY

13.1 Carcinogenesis, Mutagenesis, Impairment of Fertility

The carcinogenicity of beclomethasone dipropionate was evaluated in rats which were exposed for a total of 95 weeks: 13 weeks at inhalation doses up to 0.4 mg/kg/day and the remaining 82 weeks at combined oral and inhalation doses up to 2.4 mg/kg/day. There was no evidence of treatment-related increases in the incidence of tumors in this study at the highest dose, which is approximately 75 and 130 times the MRHD in adults and children, respectively, on a mg/m^2 basis.

Beclomethasone dipropionate did not induce gene mutation in bacterial cells or mammalian Chinese hamster ovary (CHO) cells in vitro. No significant clastogenic effect was seen in cultured CHO cells in vitro or in the mouse micronucleus test in vivo.

In rats, beclomethasone dipropionate caused decreased conception rates at an oral dose of 16 mg/kg/day (approximately 500 times the MRHD in adults on a mg/m^2 basis). Impairment of fertility, as evidenced by inhibition of the estrous cycle in dogs was observed following treatment by the oral route at a dose of 0.5 mg/kg/day (approximately 50 times the MRHD in adults on a mg/m^2 basis). No inhibition of the estrous cycle in dogs was seen following 12 months of exposure to beclomethasone dipropionate by the inhalation route at an estimated daily dose of 0.33 mg/kg (approximately 35 times the MRHD in adults on a mg/m^2 basis).

14 CLINICAL STUDIES

14.1 Seasonal and Perennial Allergic Rhinitis

Adult and Adolescent Patients Aged 12 Years and Older: The efficacy and safety of QNASL Nasal Aerosol have been evaluated in 3 randomized, double-blind, parallel-group, multicenter, placebo-controlled clinical trials of 2 to 6 weeks duration in adult and adolescent patients 12 years and older with symptoms of seasonal or perennial allergic rhinitis. The 3 clinical trials included one 2-week dose-ranging trial in patients with seasonal allergic rhinitis, one 2-week efficacy trial in patients with seasonal allergic rhinitis, and one 6-week efficacy trial in patients with perennial allergic rhinitis. The trials included a total of 1049 patients (366 males and 683 females). About 81% of patients were Caucasian and 17% African American, the mean age was approximately 38 years. Of these patients 521 received QNASL Nasal Aerosol 320 mcg once daily administered as 2 actuations in each nostril.

Assessment of efficacy was based on the total nasal symptom score (TNSS). TNSS is calculated as the sum of the patients' scoring of the 4 individual nasal symptoms (rhinorrhea, sneezing, nasal congestion, and nasal itching) on a 0 to 3 categorical severity scale (0 = absent, 1 = mild, 2 = moderate, 3 = severe) as reflective (rTNSS) or instantaneous (iTNSS). rTNSS required the patients to record symptom severity over the previous 12 hours; iTNSS required the patients to record symptom severity over the previous 10 minutes. Morning and evening TNSS scores were averaged over the treatment period and the difference from placebo in the change from baseline rTNSS was the primary efficacy endpoint. The morning iTNSS reflects the TNSS at the end of the 24-hour dosing interval and is an indication of whether the effect was maintained over the 24-hour dosing interval.

Dose-Ranging Trial: The dose-ranging trial was a 2-week trial that evaluated the efficacy of 3 doses of beclomethasone dipropionate nasal aerosol (80, 160, and 320 mcg, once daily) in patients with seasonal allergic rhinitis. In this trial, only treatment with beclomethasone dipropionate nasal aerosol at the dose of 320 mcg/day resulted in statistically significant improvements compared with placebo in the primary efficacy endpoint, rTNSS (Table 3).

Table 3. Mean Changes from Baseline in Reflective Total Nasal Symptom Score Over 2 Weeks in Adult and Adolescent Patients with Seasonal Allergic Rhinitis (ITT Population)
Treatment | N | Baseline (SD) | LS Mean (SE) Change from Baseline | Difference From Placebo
Treatment | N | Baseline (SD) | LS Mean (SE) Change from Baseline | LS Mean | 95% CI
Beclomethasone dipropionate; 320 mcg/day | 122 | 9.17 (1.66) | -2.22 (0.18) | -0.63 | -1.13, 0.13
Beclomethasone dipropionate; 160 mcg/day | 123 | 9.24 (1.57) | -1.87 (0.18) | -0.29 | -0.78, 0.21
Beclomethasone dipropionate; 80 mcg/day | 118 | 9.33 (1.72) | -1.88 (0.18) | -0.29 | -0.80, 0.21
Placebo | 123 | 8.98 (1.47) | -1.59 (0.18)

The 320 mcg dose also demonstrated a statistically significant decrease in morning iTNSS than placebo, indicating that the effect was maintained over the 24-hour dosing interval.

Seasonal and Perennial Allergic Rhinitis Trials: In 2 randomized, double-blind, parallel-group, multicenter, placebo-controlled efficacy trials, once-daily treatment with QNASL Nasal Aerosol for 2 weeks in patients with seasonal allergic rhinitis and for 6 weeks in patients with perennial allergic rhinitis resulted in statistically significant greater decreases from baseline in the rTNSS and morning iTNSS than placebo (Table 4).

Table 4. Mean Changes From Baseline in Reflective and Instantaneous Total Nasal Symptom Scores in Adult and Adolescent Patients with Seasonal or Perennial Allergic Rhinitis (ITT Population)
Treatment | N | Baseline (SD) | LS Mean (SE) Change from Baseline | Difference From Placebo
Treatment | N | Baseline (SD) | LS Mean (SE) Change from Baseline | LS Mean | 95% CI
Seasonal Allergic Rhinitis
Reflective Total Nasal Symptom Scores (rTNSS)
Beclomethasone dipropionate 320 mcg/day | 167 | 9.6 (1.51) | -2.0 (0.16) | -0.91 | -1.3, -0.5
Placebo | 171 | 9.5 (1.54) | -1.0 (0.15)
Instantaneous Total Nasal Symptom Scores (iTNSS)
Beclomethasone dipropionate 320 mcg/day | 167 | 9.0 (1.74) | -1.7 (0.15) | -0.92 | -1.3, -0.5
Placebo | 171 | 8.7 (1.81) | -0.8 (0.15)
Perennial Allergic Rhinitis
Reflective Total Nasal Symptom Scores (rTNSS)
Beclomethasone dipropionate 320 mcg/day | 232 | 8.9 (1.70) | -2.5 (0.14) | -0.84 | -1.2, -0.5
Placebo | 234 | 9.0 (1.73) | -1.6 (0.14)
Instantaneous Total Nasal Symptom Scores (iTNSS)
Beclomethasone dipropionate 320 mcg/day | 232 | 8.1 (1.98) | -2.1 (0.13) | -0.78 | -1.1, -0.4
Placebo | 234 | 8.3 (1.96) | -1.4 (0.13)

Pediatric Patients 4 to 11 Years of Age: The efficacy and safety of QNASL Nasal Aerosol have been evaluated in 2 randomized, double-blind, parallel-group, multicenter, placebo-controlled clinical trials of 2 to 12 weeks duration in pediatric patients 4 to 11 years of age with symptoms of seasonal or perennial allergic rhinitis. The 2 clinical trials included one 2-week dose-ranging trial in patients with seasonal allergic rhinitis (6 - 11 years of age), and one 12-week efficacy trial in patients with perennial allergic rhinitis (4 - 11 years of age). The trials included a total of 1255 patients (680 males and 575 females). About 73% of patients were Caucasian and 20% African American, the mean age was approximately 8 years for one study and 9 years for the second study. Of these patients 596 received QNASL Nasal Aerosol 80 mcg once daily administered as 1 actuation of QNASL 40 mcg Nasal Aerosol in each nostril.

Assessment of efficacy was based on the total nasal symptom score (TNSS) as described in adult and adolescents efficacy studies.

Dose-Ranging Seasonal Allergic Rhinitis Trial: The dose-ranging trial was a 2-week trial that evaluated the efficacy of 2 doses of beclomethasone dipropionate nasal aerosol (80 and 160 mcg, once daily) in patients with seasonal allergic rhinitis. In this trial, treatment with beclomethasone dipropionate nasal aerosol at the dose of 80 mcg/day resulted in statistically significant improvements compared with placebo in the primary efficacy endpoint, rTNSS (Table 5).

Table 5. Mean Changes from Baseline in Reflective and Instantaneous Total Nasal Symptom Scores Over 2 Weeks in Pediatric Patients with Seasonal Allergic Rhinitis (ITT Population)
Treatment | N | Baseline; (SD) | LS Mean (SE); Change; from Baseline | Difference From Placebo
Treatment | N | Baseline; (SD) | LS Mean (SE); Change; from Baseline | LS Mean | 95% CI
Reflective Total Nasal Symptom Scores (rTNSS)
Beclomethasone dipropionate 80 mcg/day | 239 | 8.9 (1.62) | -1.9 (0.14) | -0.71 | -1.1, -0.3
Beclomethasone dipropionate 160 mcg/day | 241 | 9.0 (1.71) | -2.0 (0.14) | -0.76 | -1.1, -0.4
Placebo | 234 | 9.0 (1.70) | -1.2 (0.14) | - | -; -
Instantaneous Total Nasal Symptom Scores (iTNSS)
Beclomethasone dipropionate 80 mcg/day | 238 | 8.1 (1.99) | -1.6 (0.13) | -0.63 | -1.0, -0.3
Beclomethasone dipropionate 160 mcg/day | 241 | 8.1 (2.13) | -1.7 (0.13) | -0.73 | -1.1, -0.4
Placebo | 234 | 8.2 (2.10) | -1.0 (0.13) | - | -

The 80 mcg daily dose also demonstrated a statistically significant decrease in morning iTNSS than placebo, indicating that the effect was maintained over the 24-hour dosing interval. Based on the results from the dose ranging trial, 80 mcg once daily was chosen as the dose for pediatric patients 4-11 years of age.

Perennial Allergic Rhinitis Trial: In a randomized, double-blind, parallel-group, multicenter, placebo-controlled efficacy trial, treatment with QNASL Nasal Aerosol 80 mcg once daily in patients with perennial allergic rhinitis resulted in statistically significant greater decreases from baseline in the rTNSS (the primary endpoint) and iTNSS than placebo over the first six weeks of treatment (Table 6).

Table 6. Mean Changes from Baseline in Reflective Total Nasal Symptom Score Over 6 Weeks in Pediatric Patients 6 to 11 Years of Age with Perennial Allergic Rhinitis (FAS)
Treatment | N | Baseline; (SD) | LS Mean (SE); Change from; Baseline | Difference From Placebo
Treatment | N | Baseline; (SD) | LS Mean (SE); Change from; Baseline | LS Mean | 95% CI
Reflective Total Nasal Symptom Scores (rTNSS)
Beclomethasone dipropionate 80 mcg/day | 296 | 8.6 (1.56) | -2.26 (0.12) | -0.66 | -1.08, -0.24
Placebo | 153 | 8.6 (1.60) | -1.60 (0.17) | - | -
Instantaneous Total Nasal Symptom Scores (iTNSS)
Beclomethasone dipropionate 80 mcg/day | 296 | 7.9 (2.05) | -1.98 (0.12) | -0.58 | -0.99, -0.18
Placebo | 153 | 7.8 (2.12) | -1.39 (0.17) | - | -

FAS=full analysis set

For pediatric patients 4-11 years of age, improvements in average patient-reported rTNSS and iTNSS were also significantly greater in QNASL Nasal Aerosol 80 mcg per day treated patients compared with placebo.

16 HOW SUPPLIED/STORAGE AND HANDLING

QNASL Nasal Aerosol is supplied in 2 strengths and supplied as a pressurized aluminum canister inserted into a blue and white plastic nasal actuator with a built-in dose counter and white dust cap, as follows:

QNASL 80 mcg Nasal Aerosol contains 10.6 g of drug and excipients and provides 120 actuations (NDC 59310-410-12). Each actuation delivers 80 mcg of beclomethasone dipropionate from the nasal actuator and 100 mcg from the valve.

QNASL 40 mcg Nasal Aerosol contains 6.8 g of drug and excipients and provides 60 actuations (NDC 59310-406-06). Each actuation delivers 40 mcg of beclomethasone dipropionate from the nasal actuator and 50 mcg from the valve.

Each canister of QNASL Nasal Aerosol has a dose counter, which initially reads 60 sprays or 120 sprays for the respective products, and counts down each time a spray is released. The correct amount of medication in each intranasal dose cannot be ensured after the counter reads 0; therefore, the device should be discarded when the counter reads 0.

Do not remove the QNASL Nasal Aerosol canister from the actuator. The QNASL Nasal Aerosol canister should only be used with the QNASL Nasal Aerosol actuator and the actuator should not be used with any other drug product.

CONTENTS UNDER PRESSURE

Do not puncture. Do not store near heat or open flame. Do not expose to temperatures higher than 49°C (120°F) as this may cause bursting of the canister. Never throw the device into a fire or an incinerator.

Store at temperature between 20° and 25°C (68° and 77°F); excursions are permitted between 15° and 30°C (59° and 86°F).

Keep out of reach of children.

17 PATIENT COUNSELING INFORMATION

See FDA-Approved Patient Labeling accompanying the product.

17.1 Local Nasal Effects

Inform patients that treatment with QNASL Nasal Aerosol may lead to adverse reactions, including epistaxis, nasal ulceration, and nasal discomfort. Candida infection may also occur with treatment with QNASL Nasal Aerosol. In addition, nasal beclomethasone dipropionate products are known to be associated with nasal septal perforation and impaired wound healing. Patients who have experienced recent nasal ulcers, nasal surgery, or nasal trauma should not use QNASL Nasal Aerosol until healing has occurred [see Warnings and Precautions (5.1)].

17.2 Eye Disorders

Inform patients that blurred vision, glaucoma and cataracts are associated with nasal and inhaled corticosteroid use. Patients should inform their healthcare providers if a change in vision is noted while using QNASL Nasal Aerosol [see Warnings and Precautions (5.2)].

17.3 Hypersensitivity Reactions Including Anaphylaxis

Hypersensitivity reactions including anaphylaxis, angioedema, urticaria, and rash have been reported following administration of beclomethasone dipropionate nasally administered and inhalationally administered products. Angioedema, urticaria, and rash have been reported following administration of QNASL Nasal Aerosol. If any such reactions occur, patients should discontinue use of QNASL Nasal Aerosol [see Warnings and Precautions (5.3)].

17.4 Immunosuppression

Patients who are on immunosuppressant doses of corticosteroids should be warned to avoid exposure to chickenpox or measles and, if exposed, to consult their physician without delay. Patients should be informed of potential worsening of existing tuberculosis; fungal, bacterial, viral, or parasitic infections; or ocular herpes simplex [see Warnings and Precautions (5.4)].

17.5 Use Daily for Best Effect

Patients should use QNASL Nasal Aerosol on a regular, once-daily basis since its effectiveness depends on its regular use. QNASL Nasal Aerosol may not have an immediate effect on rhinitis symptoms. The patient should not increase the prescribed dosage but should contact their physician if symptoms do not improve or if the condition worsens.

17.6 Keep Spray Out of Eyes or Mouth

Patients should be informed to avoid spraying QNASL Nasal Aerosol in their eyes or mouth.

Distributed by:

Teva Pharmaceuticals USA, Inc.

Parsippany, NJ 07054

©2020, Teva Respiratory, LLC. All rights reserved.

United States Patent No. 7,780,038

QNSPI-002

PATIENT INFORMATION

QNASL® (kyoo nay' zel)
(beclomethasone dipropionate)
Nasal Aerosol

QNASL Nasal Aerosol is available in 2 different strengths:

- QNASL Nasal Aerosol 40 mcg is only for use in children 4 years to 11 years of age and should be given under the supervision of a parent, guardian or caregiver.

- QNASL Nasal Aerosol 80 mcg is only for use in adolescents and adults 12 years of age and older.

What is QNASL Nasal Aerosol?

QNASL Nasal Aerosol is a prescription medicine that treats seasonal nasal and year-round nasal allergy symptoms in children 4 years of age and older and adults.

It is not known if QNASL Nasal Aerosol is safe and effective in children under 4 years of age.

Who should not use QNASL Nasal Aerosol?

Do not use QNASL Nasal Aerosol if you or your child is allergic to beclomethasone dipropionate or any of the ingredients in QNASL Nasal Aerosol. See the end of this leaflet for a complete list of ingredients in QNASL Nasal Aerosol.

What should you tell your or your child’s healthcare provider before using QNASL Nasal Aerosol?

Before using QNASL Nasal Aerosol, tell the healthcare provider about all of your medical conditions, including if you or your child:

- has had recent nose problems such as nasal sores, nasal surgery, or a nasal injury.
- has or have had eye problems, such as blurred vision, increased pressure in their eye (glaucoma) or cataracts.
- has tuberculosis or any untreated fungal, bacterial, or viral infections, or eye infections caused by herpes.
- has not had or been vaccinated for chickenpox or measles.
- is pregnant or plans to become pregnant. It is not known if QNASL Nasal Aerosol will harm an unborn baby. Talk to the healthcare provider if you or your child is pregnant or plans to become pregnant.
- is breastfeeding or plans to breastfeed. It is not known if QNASL Nasal Aerosol passes into breast milk. Talk to the healthcare provider about the best way to feed the baby if you or your child is using QNASL Nasal Aerosol.

Tell the healthcare provider about all of the medicines you or your child takes, including prescription and over-the-counter medicines, vitamins, and herbal supplements.

QNASL Nasal Aerosol and other medicines may affect each other and cause side effects. QNASL Nasal Aerosol may affect the way other medicines work, and other medicines may affect the way QNASL Nasal Aerosol works.

Especially tell the healthcare provider if you or your child takes other corticosteroid medicines.

Ask the healthcare provider for a list of these medicines if you are not sure.

How should you or your child use QNASL Nasal Aerosol?

- QNASL Nasal Aerosol 40 mcg is only for use in children 4 years to 11 years of age and should be given under the supervision of a parent, guardian or caregiver.
- QNASL Nasal Aerosol 80 mcg is only for use in adults and adolescents 12 years of age and older.
- Read the step-by-step Instructions for Use at the end of this leaflet for specific information about the right way to use QNASL Nasal Aerosol.
- QNASL Nasal Aerosol is for use in the nose only. Do not spray it in your eyes or mouth and do not let your child spray it in their eyes or mouth.
- Use QNASL Nasal Aerosol exactly as the healthcare provider tells you or your child to use it. Do not use more of your medicine or use it more often or let your child use more of the medicine or use it more often than the healthcare provider tells you.
- QNASL Nasal Aerosol does not need to be primed.
- QNASL Nasal Aerosol 40 mcg:
  - contains 60 sprays, and
  - has a spray counter which initially should read 60 sprays, and counts down each time a spray is released
- QNASL Nasal Aerosol 80 mcg:

- contains 120 sprays, and
- has a spray counter which initially should read 120 sprays, and counts down each time a spray is released.

- Do not use the QNASL Nasal Aerosol after the spray counter reads 0. You or your child may not get the right amount of medicine.
- The usual dose of QNASL Nasal Aerosol:

- 40 mcg is 1 spray in each nostril, 1 time a dayfor children who are 4 years to 11 years of age. Your child should not use more than a total of 2 sprays per day.

- 80 mcg is 2 sprays in each nostril, 1 time a day for adolescents and adults 12 years of age and older. You should not use more than a total of 4 sprays per day.

You and your child will get the best results if they keep using QNASL Nasal Aerosol regularly each day. If you or your child’s symptoms do not improve or get worse, call the healthcare provider.

What are the possible side effects of QNASL Nasal Aerosol?

QNASL Nasal Aerosol may cause serious side effects, including:

- ·nose bleeds or nasal ulcers. The healthcare provider should check the inside of you or your child’s nose (nasal mucosa) for problems during treatment with QNASL Nasal Aerosol. Talk to the healthcare provider if the nose bleeds or has nasal ulcers.
- fungal infections (thrush) in the nose, mouth, or throat. Tell the healthcare provider if you or your child has any redness or white colored patches in the mouth or throat.
- slow wound healing. You or your child should not use QNASL Nasal Aerosol until the nose has healed if there was a sore in the nose, if you or your child had surgery on the nose, or the nose has been injured.
- eye problems. If you or your child has had glaucoma, cataracts or blurred vision in the past, you or your child should have regular eye exams while using QNASL Nasal Aerosol. Tell the healthcare provider if you or your child has any change in vision during treatment with QNASL Nasal Aerosol.
- serious allergic reactions. Stop using QNASL Nasal Aerosol and call the healthcare provider right away or get emergency medical help right away if you or your child get any of the following signs and symptoms of a serious allergic reaction:

- hives

- swelling of your lips, tongue or face

- rash

- breathing problems

- immune system effects and a higher chance for infections. Tell your or your child’s healthcare provider about any signs or symptoms of infection such as:

- fever

- body aches

- feeling tired

- vomiting

- pain

- chills

- nausea

- reduced adrenal function (adrenal insufficiency). Adrenal insufficiency can happen in people who take higher doses of QNASL than recommended over a long period of time. Symptoms of adrenal insufficiency may include:

- feeling tired

- nausea

- weakness

- vomiting

- dizziness

- slowed growth in children. Children should have their growth checked regularly while using QNASL Nasal Aerosol.

The most common side effects with QNASL Nasal Aerosol 40 mcg in children who are 4 years to 11 years of age include:

- headache
- fever
- upper respiratory tract infection
- pain or swelling of your nose or throat (nasopharyngitis)

The most common side effects with QNASL Nasal Aerosol 80 mcg in adults and adolescents 12 years of age and older include:

- nasal discomfort
- headaches
- nose bleeds (epistaxis)

Tell the healthcare provider if you or your child has any side effect that bothers you or that does not go away.

These are not all the possible side effects of QNASL Nasal Aerosol. For more information, ask the healthcare provider or pharmacist.

Call your healthcare provider for medical advice about side effects. You may report side effects to FDA at 1-800-FDA-1088.

How should I store QNASL Nasal Aerosol?

- Store QNASL Nasal Aerosol at room temperature between 68˚F to 77˚F (20˚C to 25˚C).
- Do not puncture the QNASL Nasal Aerosol canister.
- Do not store the QNASL Nasal Aerosol canister near heat or a flame. Temperatures above 120˚F (49˚C) may cause the canister to burst.
- Do not throw the QNASL Nasal Aerosol canister into a fire or an incinerator.
- Safely throw away medicine that is out of date or no longer needed.

Keep QNASL Nasal Aerosol and all medicines out of the reach of children.

General information about the safe and effective use of QNASL Nasal Aerosol

Medicines are sometimes prescribed for purposes other than those listed in a Patient Information leaflet. Do not use QNASL Nasal Aerosol for a condition for which it was not prescribed. Do not give QNASL Nasal Aerosol to other people, even if they have the same symptoms that you or your child has. It may harm them.

You can ask your pharmacist or healthcare provider for information about QNASL Nasal Aerosol that is written for health professionals.

What are the ingredients in QNASL Nasal Aerosol?

Active ingredient: beclomethasone dipropionate

Inactive ingredient: propellant HFA-134a and dehydrated ethanol

For more information, go to www.QNASL.com or call 1-855-55-QNASL (1-855-557-6275).

Distributed by:

Teva Pharmaceuticals USA, Inc.

Parsippany, NJ 07054

© 2020, Teva Respiratory, LLC. All rights reserved.

QNSPL-002

Rev. 02/2020

PLEASE SEE REVERSE SIDE FOR INSTRUCTIONS FOR USE.

INSTRUCTIONS FOR USE

QNASL® (kyoo nay' zel) 80 mcg
(beclomethasone dipropionate)
Nasal Aerosol

Read these Instructions for Use for QNASL Nasal Aerosol before you start using it and each time you get a refill. There may be new information. This leaflet does not take the place of talking to your healthcare provider about your medical condition or treatment.

Note: For Use in the Nose Only.

- Do not spray QNASL Nasal Aerosol in your eyes, mouth or directly onto your nasal septum (the wall between your 2 nostrils).

The Parts of Your QNASL Nasal Aerosol

The QNASL Nasal Aerosol device comes as a canister that fits into a nasal actuator with a built-in spray counter and protective dust cap. (See Figure A).

- Do not use the QNASL Nasal Aerosol actuator with a canister of medicine from any other inhaler.
- Do not use the QNASL Nasal Aerosol canister with an actuator from any other inhaler.
- Do not remove the QNASL Nasal Aerosol canister from the actuator.
- When you first remove the QNASL Nasal Aerosol device from the carton, the spray counter should read “120” (See Figure B).

- You do not need to prime your QNASL Nasal Aerosol device.

Using Your QNASL Nasal Aerosol Device

Step 1: Blow your nose to clear your nostrils.

Step 2: Remove the protective dust cap from your QNASL Nasal Aerosol device by pulling it straight off.

Step 3: Inspect the nasal actuator tip to make sure it is clear of foreign objects.

Step 4: Hold your QNASL Nasal Aerosol device upright and insert the nasal actuator tip into one nostril (See Figure C).

Step 5: Point the QNASL Nasal Aerosol device slightly away from the wall between your nostrils (nasal septum) while holding your other nostril closed (See Figure D).

Step 6: Hold your breath and press down firmly and completely on the canister to release 1 spray (See Figure E). Continue to hold your breath for 5 seconds after releasing the spray and then breathe out slowly through your mouth. Take the QNASL Nasal Aerosol device out of your nostril.

Step 7: Repeat steps 3-6 for the second spray in the same nostril.

Step 8: Repeat steps 3-7 for your other nostril.

Step 9: You should not blow your nose for the next 15 minutes.

Note: The spray counter will count down each time there is a spray released from your QNASL Nasal Aerosol device.

Step 10: Clean and store your device. See "Cleaning Your QNASL Nasal Aerosol Device."

Cleaning Your QNASL Nasal Aerosol Device

- Wipe the nasal actuator tip with a clean, dry tissue or cloth (See Figure F).
- Do NOT wash or put any part of the QNASL Nasal Aerosol canister or actuator in water (See Figure G).
- Replace the protective dust cap.
- Keep your device clean and dry at all times.

How to Know When to Stop Using your QNASL Aerosol Device

- The QNASL Nasal Aerosol device has a spray counter, which is there to let you know how many sprays of medicine you have left.
- Do not use your QNASL Nasal Aerosol device when 0 is shown in the spray counter window (See Figure H).

- Throw away your QNASL Nasal Aerosol device when the spray counter reaches 0.
- Do not throw your QNASL Nasal Aerosol canister into a fire or an incinerator.
- Talk with your healthcare provider before your QNASL Nasal Aerosol medicine runs out to see if you should get a refill.

Distributed by:

Teva Pharmaceuticals USA, Inc.

Parsippany, NJ 07054

©2020 Teva Respiratory, LLC. All rights reserved.

QNSIFU80-002

Rev. 02/2020

This Patient Information and Instructions for Use has been approved by the U.S. Food and Drug Administration.

INSTRUCTIONS FOR USE

QNASL® (kyoo nay' zel) 40 mcg
(beclomethasone dipropionate)
Nasal Aerosol

Read these Instructions for Use for QNASL Nasal Aerosol before your child starts using it and each time you get a refill. There may be new information. This leaflet does not take the place of talking to the healthcare provider about your child’s medical condition or treatment.

Note: For Use in the Nose Only.

- Do not spray QNASL Nasal Aerosol in the eyes, mouth or directly onto the nasal septum (the wall between the 2 nostrils).

The Parts of Your QNASL Nasal Aerosol

The QNASL Nasal Aerosol device comes as a canister that fits into a nasal actuator with a built-in spray counter and protective dust cap. (See Figure A)

- Do not use the QNASL Nasal Aerosol actuator with a canister of medicine from any other inhaler.
- Do not use the QNASL Nasal Aerosol canister with an actuator from any other inhaler.
- Do not remove the QNASL Nasal Aerosol canister from the actuator.
- When you first remove the QNASL Nasal Aerosol device from the carton, the spray counter should read “60” (See Figure B).

- You do not need to prime the QNASL Nasal Aerosol device..

Using the QNASL Nasal Aerosol 40 mcg Device in Children 4 Years to 11 Years of Age

Children may need help from parents, guardians or caregivers.

Step 1: Have your child blow their nose to clear their nostrils.

Step 2: Remove the protective dust cap from the QNASL Nasal Aerosol device by pulling it straight off.

Step 3: Inspect the nasal actuator tip to make sure it is clear of foreign objects.

Step 4: Hold the QNASL Nasal Aerosol device upright and insert the nasal actuator tip into 1 nostril (See Figure C).

Step 5: Point the QNASL Nasal Aerosol device slightly away from the wall between the nostrils (nasal septum) while holding the other nostril closed (See Figure D).

Step 6: Have your child hold their breath and press down firmly and completely on the canister to release 1 spray (See Figure E). Continue to have your child hold their breath for 5 seconds after releasing the spray and then have them breathe out slowly through their mouth. Take the QNASL Nasal Aerosol device out of the nostril.

Step 8: Your child should not blow their nose for the next 15 minutes.

Note: The spray counter will count down each time there is a spray released from the QNASL Nasal Aerosol device.

Step 9: Clean and store the device. See "Cleaning the QNASL Nasal Aerosol Device."

Cleaning the QNASL Nasal Aerosol Device

- Wipe the nasal actuator tip with a clean, dry tissue or cloth (See Figure F).
- Do NOT wash or put any part of the QNASL Nasal Aerosol canister or actuator in water (See Figure G).
- Replace the protective dust cap.
- Keep QNASL Nasal Aerosol device clean and dry at all times.

How to Know When to Stop Using the QNASL Nasal Aerosol Device

- The QNASL Nasal Aerosol device has a spray counter, which is there to let you know how many sprays of medicine are left.
- Do not use the QNASL Nasal Aerosol device when 0 is shown in the spray counter window (See Figure H).

- Throw away the QNASL Nasal Aerosol device when the spray counter reaches 0.
- Do not throw the QNASL Nasal Aerosol canister into a fire or an incinerator.
- Talk with the healthcare provider before the QNASL Nasal Aerosol medicine runs out to see if you should get a refill.

Distributed by:

Teva Pharmaceuticals USA, Inc.

Parsippany, NJ 07054

©2020 Teva Respiratory, LLC. All rights reserved.

QNSIFU40-002

Rev. 02/2020

This Patient Information and Instructions for Use has been approved by the U.S. Food and Drug Administration.

INSTRUCTIONS FOR USE

QNASL® (kyoo nay' zel) 80 mcg
(beclomethasone dipropionate)
Nasal Aerosol

Read these Instructions for Use for QNASL Nasal Aerosol before you start using it and each time you get a refill. There may be new information. This leaflet does not take the place of talking to your healthcare provider about your medical condition or treatment.

Note: For Use in the Nose Only.

- Do not spray QNASL Nasal Aerosol in your eyes, mouth or directly onto your nasal septum (the wall between your 2 nostrils).

The parts of your QNASL Nasal Aerosol

The QNASL Nasal Aerosol device comes as a canister that fits into a nasal actuator with a built-in spray counter and protective dust cap. (See Figure A).

- Do not use the QNASL Nasal Aerosol actuator with a canister of medicine from any other inhaler.
- Do not use the QNASL Nasal Aerosol canister with an actuator from any other inhaler.
- Do not remove the QNASL Nasal Aerosol canister from the actuator.
- When you first remove the QNASL Nasal Aerosol device from the carton, the spray counter should read “120” (See Figure B).

- You do not need to prime the QNASL Nasal Aerosol device.

Using Your QNASL Nasal Aerosol Device

Step 1: Blow your nose to clear your nostrils.

Step 2: Remove the protective dust cap from your QNASL Nasal Aerosol device by pulling it straight off.

Step 3: Inspect the nasal actuator tip to make sure it is clear of foreign objects.

Step 4: Hold your QNASL Nasal Aerosol device upright and insert the nasal actuator tip into one nostril (See Figure C).

Step 5: Point the QNASL Nasal Aerosol device slightly away from the wall between your nostrils (nasal septum) while holding your other nostril closed (See Figure D).

Step 6: Hold your breath and press down firmly and completely on the canister to release 1 spray (See Figure E). Continue to hold your breath for 5 seconds after releasing the spray and then breathe out slowly through your mouth. Take the QNASL Nasal Aerosol device out of your nostril.

Step 7: Repeat steps 3-6 for the second spray in the same nostril.

Step 8: Repeat steps 3-7 for your other nostril.

Step 9: You should not blow your nose for the next 15 minutes.

Note: The spray counter will count down each time there is a spray released from your QNASL Nasal Aerosol device.

Step 10: Clean and store your device. See "Cleaning Your QNASL Nasal Aerosol device."

Cleaning Your QNASL Nasal Aerosol device

- Wipe the nasal actuator tip with a clean, dry tissue or cloth (See Figure F).
- Do NOT wash or put any part of the QNASL Nasal Aerosol canister or actuator in water (See Figure G).
- Replace the protective dust cap.
- Keep your device clean and dry at all times.

How to know when to stop using your QNASL Aerosol device

- The QNASL Nasal Aerosol device has a spray counter, which is there to let you know how many sprays of medicine you have left.
- Do not use your QNASL Nasal Aerosol device when 0 is shown in the spray counter window (See Figure H).

- Throw away your QNASL Nasal Aerosol device when the spray counter reaches 0.
- Do not throw your QNASL Nasal Aerosol canister into a fire or an incinerator.
- Talk with your healthcare provider before your QNASL Nasal Aerosol medicine runs out to see if you should get a refill.

Manufactured for:

Teva Respiratory, LLC

Frazer, PA 19355

By:

Norton (Waterford) Limited

Unit 301, IDA Industrial Park, Cork Road

Waterford, Ireland

©2018 Teva Respiratory, LLC

All rights reserved.

QNSIFU80-001

Rev. 03/2018

This Patient Information and Instructions for Use has been approved by the U.S. Food and Drug Administration.

INSTRUCTIONS FOR USE

QNASL® (kyoo nay' zel) 40 mcg
(beclomethasone dipropionate)
Nasal Aerosol

Read these Instructions for Use for QNASL Nasal Aerosol before your child starts using it and each time you get a refill. There may be new information. This leaflet does not take the place of talking to the healthcare provider about your child’s medical condition or treatment.

Note: For Use in the Nose Only.

- Do not spray QNASL Nasal Aerosol in the eyes, mouth or directly onto the nasal septum (the wall between the 2 nostrils).

The parts of your QNASL Nasal Aerosol

The QNASL Nasal Aerosol device comes as a canister that fits into a nasal actuator with a built-in spray counter and protective dust cap. (See Figure A)

- Do not use the QNASL Nasal Aerosol actuator with a canister of medicine from any other inhaler.
- Do not use the QNASL Nasal Aerosol canister with an actuator from any other inhaler.
- Do not remove the QNASL Nasal Aerosol canister from the actuator.
- When you first remove the QNASL Nasal Aerosol device from the carton, the spray counter should read “60” (See Figure B).

- You do not need to prime the QNASL Nasal Aerosol device.

Using the QNASL Nasal Aerosol 40 mcg device in Children 4 years to 11 Years of Age

Children may need help from parents, guardians or caregivers.

Step 1: Have your child blow their nose to clear their nostrils.

Step 2: Remove the protective dust cap from the QNASL Nasal Aerosol device by pulling it straight off.

Step 3: Inspect the nasal actuator tip to make sure it is clear of foreign objects.

Step 4: Hold the QNASL Nasal Aerosol device upright and insert the nasal actuator tip into 1 nostril (See Figure C).

Step 5: Point the QNASL Nasal Aerosol device slightly away from the wall between the nostrils (nasal septum) while holding the other nostril closed (See Figure D).

Step 6: Have your child hold their breath and press down firmly and completely on the canister to release 1 spray (See Figure E). Continue to have your child hold their breath for 5 seconds after releasing the spray and then have them breathe out slowly through their mouth. Take the QNASL Nasal Aerosol device out of the nostril.

Step 7: Repeat steps 3-6 for the other nostril.

Step 8: Your child should not blow their nose for the next 15 minutes.

Note: The spray counter will count down each time there is a spray released from the QNASL Nasal Aerosol device.

Step 9: Clean and store the device. See "Cleaning the QNASL Nasal Aerosol device."

Cleaning the QNASL Nasal Aerosol device

- Wipe the nasal actuator tip with a clean, dry tissue or cloth (See Figure F).
- Do NOT wash or put any part of the QNASL Nasal Aerosol canister or actuator in water (See Figure G).
- Replace the protective dust cap.
- Keep QNASL Nasal Aerosol device clean and dry at all times.

How to know when to stop using the QNASL Nasal Aerosol device

- The QNASL Nasal Aerosol device has a spray counter, which is there to let you know how many sprays of medicine are left.
- Do not use the QNASL Nasal Aerosol device when 0 is shown in the spray counter window (See Figure H).

- Throw away the QNASL Nasal Aerosol device when the spray counter reaches 0.
- Do not throw the QNASL Nasal Aerosol canister into a fire or an incinerator.
- Talk with the healthcare provider before the QNASL Nasal Aerosol medicine runs out to see if you should get a refill.

Manufactured for:

Teva Respiratory, LLC

Frazer, PA 19355

By:

Norton (Waterford) Limited

Unit 301, IDA Industrial Park, Cork Road

Waterford, Ireland

©2018 Teva Respiratory, LLC

All rights reserved.

QNSIFU40-001

Rev. 03/2018

This Patient Information and Instructions for Use has been approved by the U.S. Food and Drug Administration.

80 mcg Trade Carton Display Panel

NDC 59310-410-12

Qnasl®

(beclomethasone diproprionate) Nasal Aerosol

80 mcg per spray

No Priming Required

For Intranasal Use with Qnasl Actuator Only

Rx only

120 Metered Sprays
10.6 g Net Contents

TEVA

40 mcg Trade Carton Display Panel

NDC 59310-406-06

Children’s Qnasl® 40 mcg

(beclomethasone diproprionate)

Nasal Aerosol 40 mcg per spray

No Priming Required

For Intranasal Use with Qnasl Actuator Only

Rx only

60 Metered Sprays
6.8 g Net Contents

TEVA

40 mcg Sample Carton Display Panel

NDC 59310-406-08

Children’s Qnasl® 40 mcg

(beclomethasone diproprionate)

Nasal Aerosol 40 mcg per spray

No Priming Required

Professional Sample Not for Sale or Reimbursement

For Intranasal Use with Qnasl Actuator Only

Rx only

60 Metered Sprays
6.8 g Net Contents

TEVA

80 mcg Sample Carton Display Panel

NDC 59310-410-13

Qnasl®

(beclomethasone diproprionate)

Nasal Aerosol 80 mcg per spray

No Priming Required

Professional Sample Not for Sale or Reimbursement

For Intranasal Use with Qnasl Actuator Only

Rx only

50 Metered Sprays
6.8 g Net Contents

TEVA